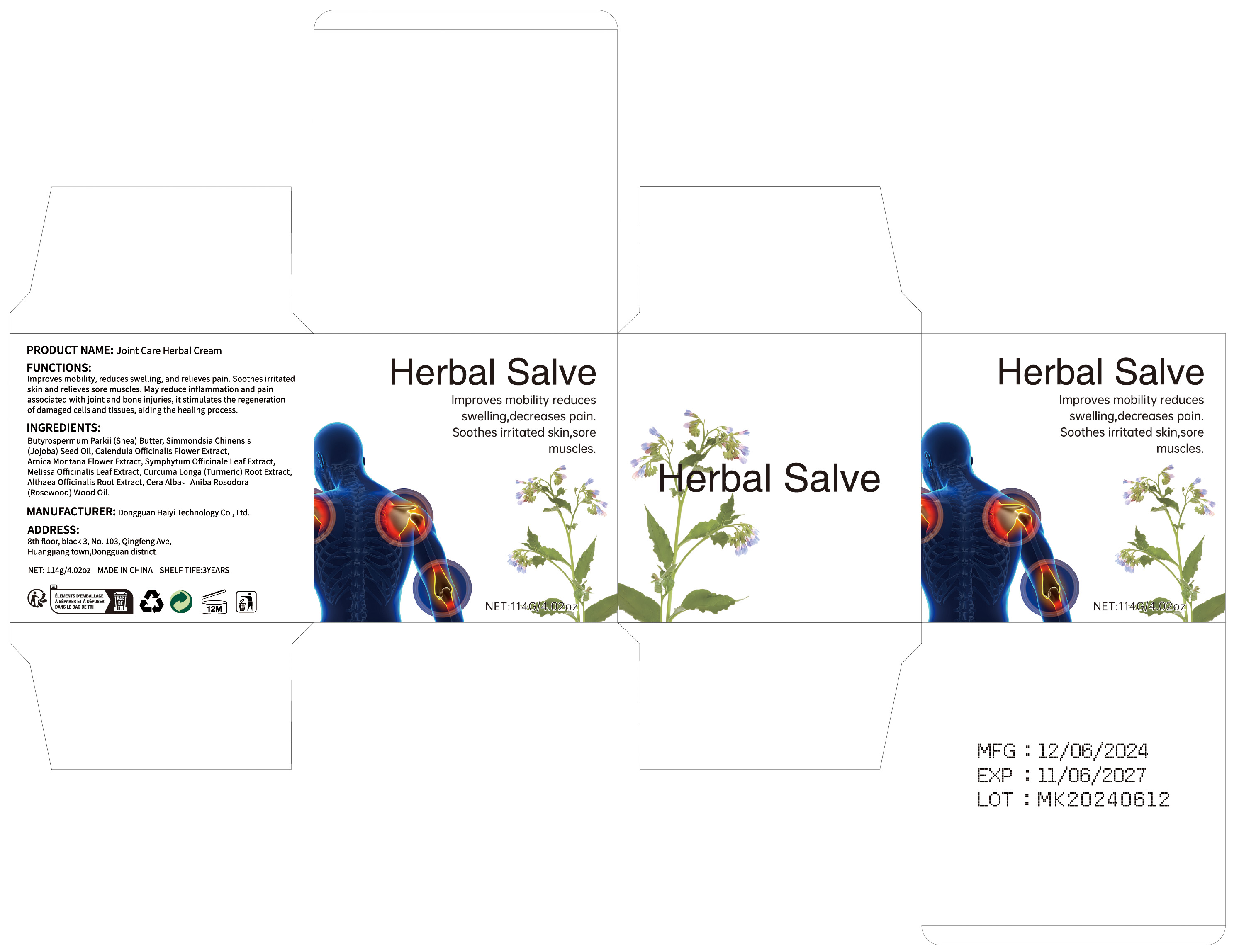 DRUG LABEL: Joint Care Herbal Cream
NDC: 84732-088 | Form: CREAM
Manufacturer: Dongguan Haiyi Technology Co.,Ltd.
Category: otc | Type: HUMAN OTC DRUG LABEL
Date: 20241106

ACTIVE INGREDIENTS: COMFREY LEAF 1 mg/100 g
INACTIVE INGREDIENTS: MELISSA OFFICINALIS LEAF; CARYA TOMENTOSA BARK; BRAZILIAN ROSEWOOD OIL; SHEA BUTTER; JOJOBA OIL; CURCUMA LONGA (TURMERIC) ROOT EXTRACT; ALTHAEA OFFICINALIS ROOT; ARNICA MONTANA FLOWER; CALENDULA OFFICINALIS FLOWER

Active ingredient

Butyrospermum Parkii (Shea) Butter

Inactive ingredient

Simmondsia Chinensis(Jojoba) Seed Oil, Calendula Officinalis Flower Extract,Arnica Montana Flower Extract, Symphytum Officinale Leaf Extract,Melissa Officinalis Leaf Extract, Curcuma Longa (Turmeric) Root Extract,Althaea Officinalis Root Extract, Cera Alba、 Aniba Rosodora(Rosewood) Wood Oil.

Purpose section

Improves mobility, reduces swelling, and relieves pain. Soothes irritated skin and relieves sore muscles, May reduce inflammation and pain associated with joint and bone injuries, it stimulates the regeneration of damaged cells and tissues, aiding the healing process.

Warning

1).For external use only, avoid directcontact with eyes, lf you feel any
discomfort, stop using itand wash it with plenty of water. In severe cases,
pleaseseek medical attention in time.
2). Not allowed to be used ondamaged skin,

stop use

This product may cause allergic reactions in asmall number of people.
lf youexperience any discomfort,please stop using it immediately.

not use

Not suitable for use by children, pregnantor breast feeding people.

OUT OF CHILDREN

KEEP THE PRODUCT OUT OF REACH OF CHILDREN to

HOW TO USE

Apply to painful areas of the body

Dosage

take an appropriateamount,Use 2-3 times a week